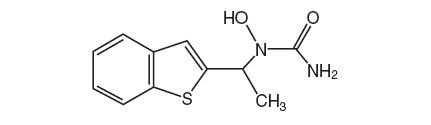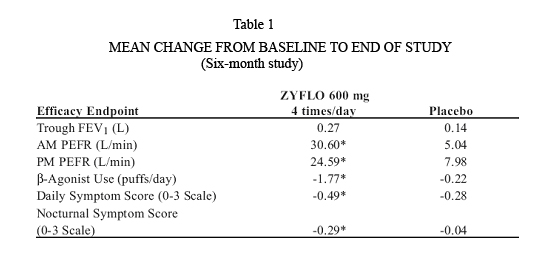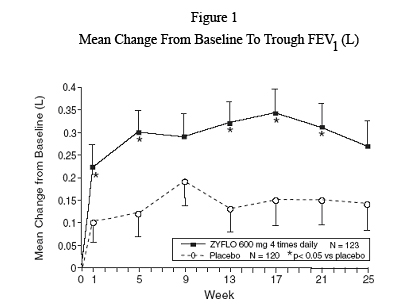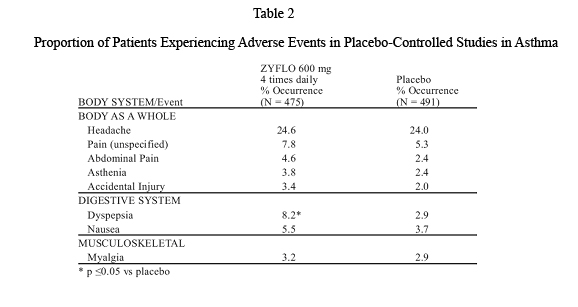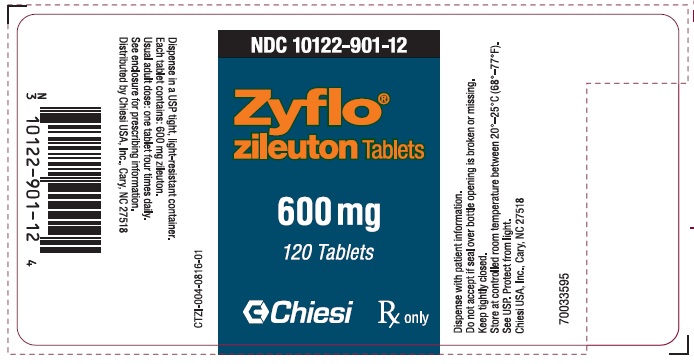 DRUG LABEL: ZYFLO
NDC: 10122-901 | Form: TABLET
Manufacturer: Chiesi USA, Inc.
Category: prescription | Type: HUMAN PRESCRIPTION DRUG LABEL
Date: 20251130

ACTIVE INGREDIENTS: ZILEUTON 600 mg/1 1
INACTIVE INGREDIENTS: CROSPOVIDONE; HYDROXYPROPYL CELLULOSE (1600000 WAMW); HYPROMELLOSES; MAGNESIUM STEARATE; CELLULOSE, MICROCRYSTALLINE; PROPYLENE GLYCOL; SODIUM STARCH GLYCOLATE TYPE A POTATO; TALC; TITANIUM DIOXIDE; STARCH, CORN

Zyflo

DESCRIPTION

Zileuton is an orally active inhibitor of 5-lipoxygenase, the enzyme that catalyzes the formation of leukotrienes from arachidonic acid. Zileuton has the chemical name (±)-1-(1-Benzo[b]thien-2-ylethyl)-1-hydroxyurea and the following chemical structure:

Zileuton

Zileuton has the molecular formula C11H12N2O2S and a molecular weight of 236.29. It is a racemic mixture (50:50) of R(+) and S(-) enantiomers. Zileuton is a practically odorless, white, crystalline powder that is soluble in methanol and ethanol, slightly soluble in acetonitrile, and practically insoluble in water and hexane. The melting point ranges from 144.2˚C to 145.2˚C. ZYFLO tablets for oral administration are supplied in one dosage strength containing 600 mg of zileuton.

Inactive Ingredients: crospovidone, hydroxypropyl cellulose, hypromellose, magnesium stearate, microcrystalline cellulose, pregelatinized starch, propylene glycol, sodium starch glycolate, talc, and titanium dioxide.

CLINICAL PHARMACOLOGY

Mechanism of Action:

Zileuton is a specific inhibitor of 5-lipoxygenase and thus inhibits leukotriene (LTB4, LTC4, LTD4, and LTE4) formation. Both the R(+) and S(-) enantiomers are pharmacologically active as 5-lipoxygenase inhibitors in in vitro systems. Leukotrienes are substances that induce numerous biological effects including augmentation of neutrophil and eosinophil migration, neutrophil and monocyte aggregation, leukocyte adhesion, increased capillary permeability, and smooth muscle contraction. These effects contribute to inflammation, edema, mucus secretion, and bronchoconstriction in the airways of asthmatic patients. Sulfido-peptide leukotrienes (LTC4, LTD4, LTE4, also known as the slow-releasing substances of anaphylaxis) and LTB4, a chemoattractant for neutrophils and eosinophils, can be measured in a number of biological fluids including bronchoalveolar lavage fluid (BALF) from asthmatic patients.

Zileuton is an orally active inhibitor of ex vivo LTB4 formation in several species, including dogs, monkeys, rats, sheep, and rabbits. Zileuton inhibits arachidonic acid-induced ear edema in mice, neutrophil migration in mice in response to polyacrylamide gel, and eosinophil migration into the lungs of antigen-challenged sheep.

Zileuton inhibits leukotriene-dependent smooth muscle contractions in vitro in guinea pig and human airways. The compound inhibits leukotriene-dependent bronchospasm in antigen and arachidonic acid-challenged guinea pigs. In antigen-challenged sheep, zileuton inhibits late-phase bronchoconstriction and airway hyperreactivity. In humans, pretreatment with zileuton attenuated bronchoconstriction caused by cold air challenge in patients with asthma.

PHARMACOKINETICS

Zileuton is rapidly absorbed upon oral administration with a mean time to peak plasma concentration (Tmax) of 1.7 hours and a mean peak level (Cmax) of 4.98 μg/mL. The absolute bioavailability of ZYFLO is unknown. Systemic exposure (mean AUC) following 600 mg ZYFLO administration is 19.2 μg.hr/mL. Plasma concentrations of zileuton are proportional to dose, and steady-state levels are predictable from single-dose pharmacokinetic data. Administration of ZYFLO with food resulted in a small but statistically significant increase (27%) in zileuton Cmax without significant changes in the extent of absorption (AUC) or Tmax. Therefore, ZYFLO can be administered with or without food (see DOSAGE AND ADMINISTRATION).

The apparent volume of distribution (V/F) of zileuton is approximately 1.2 L/kg. Zileuton is 93% bound to plasma proteins, primarily to albumin, with minor binding to αl-acid glycoprotein.

Elimination of zileuton is predominantly via metabolism with a mean terminal half-life of 2.5 hours. Apparent oral clearance of zileuton is 7.0 mL/min/kg. ZYFLO activity is primarily due to the parent drug. Studies with radiolabeled drug demonstrated that orally administered zileuton is well absorbed into the systemic circulation with 94.5% and 2.2% of the radiolabeled dose recovered in urine and feces, respectively. Several zileuton metabolites have been identified in human plasma and urine. These include two diastereomeric O-glucuronide conjugates (major metabolites) and an N-dehydroxylated metabolite of zileuton. The urinary excretion of the inactive N-dehydroxylated metabolite and unchanged zileuton each accounted for less than 0.5% of the dose. In vitro studies utilizing human liver microsomes have shown that zileuton and its N-dehydroxylated metabolite can be oxidatively metabolized by the cytochrome P450 isoenzymes 1A2, 2C9 and 3A4 (CYP1A2, CYP2C9 and CYP3A4).

Special populations:

Effect of age: The pharmacokinetics of zileuton were investigated in healthy elderly volunteers (ages 65 to 81 years, 9 males, 9 females) and healthy young volunteers (ages 20 to 40 years, 5 males and 4 females) after single and multiple oral doses of 600 mg every 6 hours of zileuton. Zileuton pharmacokinetics were similar in healthy elderly subjects (≥65 years) compared to healthy younger adults (18 to 40 years).

Effect of gender: Across several studies, no significant gender effects were observed on the pharmacokinetics of zileuton.

Renal insufficiency: The pharmacokinetics of zileuton were similar in healthy subjects and in subjects with mild, moderate, and severe renal insufficiency. In subjects with renal failure requiring hemodialysis, zileuton pharmacokinetics were not altered by hemodialysis and a very small percentage of the administered zileuton dose (<0.5%) was removed by hemodialysis. Hence, dosing adjustment in patients with renal dysfunction or undergoing hemodialysis is not necessary.

Hepatic insufficiency: ZYFLO is contraindicated in patients with active liver disease (see CONTRAINDICATIONS and PRECAUTIONS, Hepatic).

CLINICAL STUDIES

Two double-blind, parallel, placebo-controlled, multi-center studies have established the efficacy of ZYFLO in the treatment of asthma. Three hundred seventy-three (373) patients were enrolled in the 6-month, double-blind phase of Study 1, and 401 patients were enrolled in the 3-month double-blind phase of Study 2. In these studies, the patients were mild-to-moderate asthmatics who had a mean baseline FEV1 of approximately 2.3 liters and who used inhaled beta-agonists as needed, the mean being approximately 6 puffs of albuterol per day from a metered-dose inhaler. In each study, patients were randomized to receive either ZYFLO 400 mg four times daily, ZYFLO 600 mg four times daily, or placebo. Only the ZYFLO 600 mg four times daily dosage regimen was shown to be efficacious by demonstrating statistically significant improvement across several parameters.

Efficacy endpoints measured in Study 1 are shown in Table 1 below as mean change from baseline to the end of the study (six months). Statistically significant differences from placebo at the p<0.05 level are indicated by an asterisk(*). Similar results were observed after three months in Study 2.

Mean Change from Baseline to End of Study

Figure 1 shows the mean effect of ZYFLO versus placebo for the primary efficacy variable, trough FEV1, over the course of Study 1.

Mean Change From Baseline to Trough FEV1 (L)

Of all the patients in Study 1 and Study 2, 7.0% of those administered ZYFLO 600 mg four times daily required systemic corticosteroid therapy for exacerbation of asthma, whereas 18.7% of the placebo group required corticosteroid treatment. This difference was statistically significant.

In these trials, there was a statistically significant improvement from baseline in FEV1, which occurred 2 hours after initial administration of ZYFLO. This mean increase was approximately 0.10 L greater than that in placebo-treated patients.

These studies evaluated patients receiving as-needed inhaled beta-agonist as their only asthma therapy. In this patient population, post-hoc analyses suggested that individuals with lower FEV1 values at baseline showed a greater improvement.

The role of ZYFLO in the management of patients with more severe asthma, patients receiving anti-asthma therapy other than as-needed, inhaled beta-agonists, or patients receiving it as an oral or inhaled corticosteroid-sparing agent remains to be fully characterized.

INDICATIONS AND USAGE

ZYFLO is indicated for the prophylaxis and chronic treatment of asthma in adults and children 12 years of age and older.

CONTRAINDICATIONS

ZYFLO tablets are contraindicated in patients with:

- Active liver disease or transaminase elevations greater than or equal to three times the upper limit of normal (≥3xULN) (see PRECAUTIONS, Hepatic).
- Hypersensitivity to zileuton or any of its inactive ingredients.

WARNINGS

ZYFLO is not indicated for use in the reversal of bronchospasm in acute asthma attacks, including status asthmaticus. Therapy with ZYFLO can be continued during acute exacerbations of asthma.

Co-administration of ZYFLO and theophylline results in, on average, an approximate doubling of serum theophylline concentrations. Theophylline dosage in these patients should be reduced and serum theophylline concentrations monitored closely (see PRECAUTIONS, Drug Interactions).

Co-administration of ZYFLO and warfarin results in a clinically significant increase in prothrombin time (PT). Patients on oral warfarin therapy and ZYFLO should have their prothrombin times monitored closely and anticoagulant dose adjusted accordingly (see PRECAUTIONS, Drug Interactions).

Co-administration of ZYFLO and propranolol results in doubling of propranolol AUC and consequent increased beta-blocker activity. Patients on ZYFLO and propranolol should be closely monitored and the dose of the propranolol reduced as necessary (see PRECAUTIONS, Drug Interactions).

PRECAUTIONS

Hepatic:

Elevations of one or more liver function tests may occur during ZYFLO therapy. These laboratory abnormalities may progress, remain unchanged, or resolve with continued therapy. In a few cases, initial transaminase elevations were first noted after discontinuing treatment, usually within 2 weeks. The ALT (SGPT) test is considered the most sensitive indicator of liver injury. In placebo-controlled clinical trials, the frequency of ALT elevations greater than or equal to three times the upper limit of normal (3xULN) was 1.9% for ZYFLO-treated patients, compared with 0.2% for placebo-treated patients.

In a long-term safety surveillance study, 2458 patients received ZYFLO in addition to their usual asthma care and 489 received their usual asthma care. In patients treated for up to 12 months with ZYFLO in addition to their usual asthma care, 4.6% developed an ALT of at least 3xULN, compared with 1.1% of patients receiving only their usual asthma care. Sixty-one percent of these elevations occurred during the first two months of ZYFLO therapy. After two months of treatment, the rate of new ALT elevations ≥3xULN stabilized at a mean of 0.30% per month for patients receiving ZYFLO-plus-usual-asthma care compared with 0.11% per month for patients receiving usual asthma care alone. Of the 61 ZYFLO plus-usual-asthma-care patients with ALT elevations between 3 to 5xULN, 32 patients (52%) had ALT values decrease to below 2xULN while continuing ZYFLO therapy. Twenty-one of the 61 patients (34%) had further increases in ALT levels to ≥5xULN and were withdrawn from the study in accordance with the study protocol. In patients who discontinued ZYFLO, elevated ALT levels returned to <2xULN in an average of 32 days (range 1-111 days).

In controlled and uncontrolled clinical trials involving more than 5000 patients treated with ZYFLO, the overall rate of ALT elevation ≥3xULN was 3.2%. In these trials, one patient developed symptomatic hepatitis with jaundice, which resolved upon discontinuation of therapy. An additional 3 patients with transaminase elevations developed mild hyperbilirubinemia that was less than three times the upper limit of normal. There was no evidence of hypersensitivity or other alternative etiologies for these findings. In subset analyses, females over the age of 65 appeared to be at an increased risk for ALT elevations. Patients with pre-existing transaminase elevations may also be at an increased risk for ALT elevations (see CONTRAINDICATIONS).

It is recommended that hepatic transaminases be evaluated at initiation of, and during therapy with, ZYFLO. Serum ALT should be monitored before treatment begins, once-a-month for the first 3 months, every two to three months for the remainder of the first year, and periodically thereafter for patients receiving long-term ZYFLO therapy. If clinical signs and/or symptoms of liver dysfunction (e.g., right upper quadrant pain, nausea, fatigue, lethargy, pruritus, jaundice, or “flu-like” symptoms) develop or transaminase elevations greater than 5 times the ULN occur, ZYFLO should be discontinued and transaminase levels followed until normal.

Since treatment with ZYFLO may result in increased hepatic transaminases, ZYFLO should be used with caution in patients who consume substantial quantities of alcohol and/or have a past history of liver disease.

Neuropsychiatric Events:

Neuropsychiatric events have been reported in adult and adolescent patients taking zileuton, the active ingredient in ZYFLO and zileuton extended-release tablets. Post-marketing reports with zileuton include sleep disorders and behavior changes. The clinical details of some post-marketing reports involving ZYFLO appear consistent with a drug-induced effect. Patients and prescribers should be alert for neuropsychiatric events. Patients should be instructed to notify their prescriber if these changes occur. Prescribers should carefully evaluate the risks and benefits of continuing treatment with ZYFLO if such events occur (see ADVERSE REACTIONS, Post-marketing Experience).

Information for Patients:

Patients should be told that:

- ZYFLO is indicated for the chronic treatment of asthma and should be taken regularly as prescribed, even during symptom-free periods.
- ZYFLO is not a bronchodilator and should not be used to treat acute episodes of asthma.
- When taking ZYFLO, they should not decrease the dose or stop taking any other antiasthma medications unless instructed by a physician.
- While using ZYFLO, medical attention should be sought if short-acting bronchodilators are needed more often than usual, or if more than the maximum number of inhalations of short-acting bronchodilator treatment prescribed for a 24-hour period are needed.
- The most serious side effect of ZYFLO is elevation of liver enzyme tests and that, while taking ZYFLO, they must return for liver enzyme test monitoring on a regular basis.
- If they experience signs and/or symptoms of liver dysfunction (e.g., right upper quadrant pain, nausea, fatigue, lethargy, pruritus, jaundice, or “flu-like” symptoms), they should contact their physician immediately.
- Patients should be instructed to notify their healthcare provider if neuropsychiatric events occur while using ZYFLO.
- ZYFLO can interact with other drugs and that, while taking ZYFLO, they should consult their doctor before starting or stopping any prescription or non-prescription medicines.

A patient leaflet is included with the tablets.

Drug Interactions:

In a drug-interaction study in 16 healthy volunteers, co-administration of multiple doses of zileuton (800 mg every 12 hours) and theophylline (200 mg every 6 hours) for 5 days resulted in a significant decrease (approximately 50%) in steady-state clearance of theophylline, an approximate doubling of theophylline AUC, and an increase in theophylline Cmax (by 73%). The elimination half-life of theophylline was increased by 24%. Also, during co-administration, theophylline-related adverse events were observed more frequently than after theophylline alone. Upon initiation of ZYFLO in patients receiving theophylline, the theophylline dosage should be reduced by approximately one-half and plasma theophylline concentrations monitored. Similarly, when initiating therapy with theophylline in a patient receiving ZYFLO, the maintenance dose and/or dosing interval of theophylline should be adjusted accordingly and guided by serum theophylline determinations (see WARNINGS).

Concomitant administration of multiple doses of ZYFLO (600 mg every 6 hours) and warfarin (fixed daily dose obtained by titration in each subject) to 30 healthy male volunteers resulted in a 15% decrease in R-warfarin clearance and an increase in AUC of 22%. The pharmacokinetics of S-warfarin were not affected. These pharmacokinetic changes were accompanied by a clinically significant increase in prothrombin times. Monitoring of prothrombin time, or other suitable coagulation tests, with the appropriate dose titration of warfarin is recommended in patients receiving concomitant ZYFLO and warfarin therapy (see WARNINGS).

Co-administration of ZYFLO and propranolol results in a significant increase in propranolol concentrations. Administration of a single 80-mg dose of propranolol in 16 healthy male volunteers who received ZYFLO 600 mg every 6 hours for 5 days resulted in a 42% decrease in propranolol clearance. This resulted in an increase in propranolol Cmax, AUC, and elimination half-life by 52%, 104%, and 25%, respectively. There was an increase in β-blockade and decrease in heart rate associated with the co-administration of these drugs. Patients on ZYFLO and propranolol should be closely monitored and the dose of propranolol reduced as necessary (see WARNINGS). No formal drug-drug interaction studies between ZYFLO and other beta-adrenergic blocking agents (i.e., β-blockers) have been conducted. It is reasonable to employ appropriate clinical monitoring when these drugs are co-administered with ZYFLO.

In a drug interaction study in 16 healthy volunteers, co-administration of multiple doses of terfenadine (60 mg every 12 hours) and ZYFLO (600 mg every 6 hours) for 7 days resulted in a decrease in clearance of terfenadine by 22% leading to a statistically significant increase in mean AUC and Cmax of terfenadine of approximately 35%. This increase in terfenadine plasma concentration in the presence of ZYFLO was not associated with a significant prolongation of the QTc interval. Although there was no cardiac effect in this small number of healthy volunteers, given the high inter-individual pharmacokinetic variability of terfenadine, co-administration of ZYFLO and terfenadine is not recommended.

Drug-drug interaction studies conducted in healthy volunteers between ZYFLO and prednisone and ethinyl estradiol (oral contraceptive), drugs known to be metabolized by the P450 3A4 (CYP3A4) isoenzyme, have shown no significant interaction. However, no formal drug-drug interaction studies between ZYFLO and dihydropyridine, calcium channel blockers, cyclosporine, cisapride, and astemizole, also metabolized by CYP3A4, have been conducted. It is reasonable to employ appropriate clinical monitoring when these drugs are co-administered with ZYFLO.

Drug-drug interaction studies in healthy volunteers have been conducted with ZYFLO and digoxin, phenytoin, sulfasalazine, and naproxen. There was no significant interaction between ZYFLO and any of these drugs.

Carcinogenesis, Mutagenesis, Impairment of Fertility:

In 2-year carcinogenicity studies, increases in the incidence of liver, kidney, and vascular tumors in female mice and a trend towards an increase in the incidence of liver tumors in male mice were observed at 450 mg/kg/day (providing approximately 4 times [females] or 7 times [males] the systemic exposure [AUC] achieved at the maximum recommended human daily oral dose). No increase in the incidence of tumors was observed at 150 mg/kg/day (providing approximately 2 times the systemic exposure [AUC] achieved at the maximum recommended human daily oral dose). In rats, an increase in the incidence of kidney tumors was observed in both sexes at 170 mg/kg/day (providing approximately 6 times [males] or 14 times [females] the systemic exposure [AUC] achieved at the maximum recommended human daily oral dose). No increased incidence of kidney tumors was seen at 80 mg/kg/day (providing approximately 4 times [males] or 6 times [females] the systemic exposure [AUC] achieved at the maximum recommended human daily oral dose). Although a dose-related increased incidence of benign Leydig cell tumors was observed, Leydig cell tumorigenesis was prevented by supplementing male rats with testosterone.

Zileuton was negative in genotoxicity studies including bacterial reverse mutation (Ames) using S. typhimurium and E. coli, chromosome aberration in human lymphocytes, in vitro unscheduled DNA synthesis (UDS), in rat hepatocytes with or without zileuton pretreatment and in mouse and rat kidney cells with zileuton pretreatment, and mouse micronucleus assays. However, a dose-related increase in DNA adduct formation was reported in kidneys and livers of female mice treated with zileuton. Although some evidence of DNA damage was observed in a UDS assay in hepatocytes isolated from Aroclor-1254 treated rats, no such finding was noticed in hepatocytes isolated from monkeys, where the metabolic profile of zileuton is more similar to that of humans.

In reproductive performance/fertility studies, zileuton produced no effects on fertility in rats at oral doses up to 300 mg/kg/day (providing approximately 8 times [male rats] and 18 times [female rats] the systemic exposure [AUC] achieved at the maximum recommended human daily oral dose). Comparative systemic exposure (AUC) is based on measurements in male rats or nonpregnant female rats at similar dosages. However, reduction in fetal implants was observed at oral doses of 150 mg/kg/day and higher (providing approximately 9 times the systemic exposure [AUC] achieved at the maximum recommended human daily oral dose). Increases in gestation length, prolongation of estrous cycle, and increases in stillbirths were observed at oral doses of 70 mg/kg/day and higher (providing approximately 4 times the systemic exposure (AUC) achieved at the maximum recommended human daily oral dose). In a perinatal/postnatal study in rats, reduced pup survival and growth were noted at an oral dose of 300 mg/kg/day (providing approximately 18 times the systemic exposure [AUC] achieved at the maximum recommended human daily oral dose).

Pregnancy: Pregnancy Category C: Developmental studies indicated adverse effects (reduced body weight and increased skeletal variations) in rats at an oral dose of 300 mg/kg/day (providing approximately 18 times the systemic exposure [AUC] achieved at the maximum recommended human daily oral dose). Comparative systemic exposure [AUC] is based on measurements in nonpregnant female rats at a similar dosage. Zileuton and/or its metabolites cross the placental barrier of rats. Three of 118 (2.5%) rabbit fetuses had cleft palates at an oral dose of 150 mg/kg/day (equivalent to the maximum recommended human daily oral dose on a mg/m^2 basis). There are no adequate and well-controlled studies in pregnant women. ZYFLO should be used during pregnancy only if the potential benefit justifies the potential risk to the fetus.

Nursing Mothers: Zileuton and/or its metabolites are excreted in rat milk. It is not known if zileuton is excreted in human milk. Because many drugs are excreted in human milk, and because of the potential for tumorigenicity shown for ZYFLO in animal studies, a decision should be made whether to discontinue nursing or to discontinue the drug, taking into account the importance of the drug to the mother.

Pediatric Use: The safety and effectiveness of ZYFLO in pediatric patients under 12 years of age have not been established. Due to the risk of hepatoxicity, use of ZYFLO in pediatric patients under 12 years of age is not recommended.

Geriatric Use: In subset analyses, females over the age of 65 appeared to be at an increased risk for ALT elevations. Zileuton pharmacokinetics were similar in healthy elderly subjects (≥65 years) compared to healthy younger adults (18 to 40 years) (see PHARMACOKINETICS-- Special populations: Effect of age).

ADVERSE REACTIONS

Clinical Studies:

A total of 5542 patients have been exposed to zileuton in clinical trials, 2252 of them for greater than 6 months and 742 for greater than 1 year.

Adverse events most frequently occurring (frequency ≥3%) in ZYFLO-treated patients and at a frequency greater than placebo-treated patients are summarized in Table 2.

Proportion of Patients Experiencing Adverse Events in Placebo-Controlled Studies in Asthma

Less common adverse events occurring at a frequency of greater than 1% and more commonly in ZYFLO-treated patients included: arthralgia, chest pain, conjunctivitis, constipation, dizziness, fever, flatulence, hypertonia, insomnia, lymphadenopathy, malaise, neck pain/rigidity, nervousness, pruritus, somnolence, urinary tract infection, vaginitis, and vomiting.

The frequency of discontinuation from the asthma clinical studies due to any adverse event was comparable between ZYFLO (9.7%) and placebo-treated (8.4%) groups.

In placebo-controlled clinical trials, the frequency of ALT elevations ≥3xULN was 1.9% for ZYFLO-treated patients, compared with 0.2% for placebo-treated patients. In controlled and uncontrolled trials, one patient developed symptomatic hepatitis with jaundice, which resolved upon discontinuation of therapy. An additional 3 patients with transaminase elevations developed mild hyperbilirubinemia that was less than three times the upper limit of normal. There was no evidence of hypersensitivity or other alternative etiologies for these findings. ZYFLO is contraindicated in patients with active liver disease or transaminase elevations greater than or equal to 3xULN (see CONTRAINDICATIONS). It is recommended that hepatic transaminases be evaluated at initiation of and during therapy with ZYFLO (see PRECAUTIONS, Hepatic).

Occurrences of low white blood cell count (≤2.8 x 10^9/L) were observed in 1.0% of 1,678 patients taking ZYFLO and 0.6% of 1,056 patients taking placebo in placebo-controlled studies. These findings were transient and the majority of cases returned toward normal or baseline with continued ZYFLO dosing. All remaining cases returned toward normal or baseline after discontinuation of ZYFLO. Similar findings were also noted in a long-term safety surveillance study of 2458 patients treated with ZYFLO plus usual asthma care versus 489 patients treated only with usual asthma care for up to one year. The clinical significance of these observations is not known.

In the long-term safety surveillance trial of ZYFLO plus usual asthma care versus usual asthma care alone, a similar adverse event profile was seen as in other clinical trials.

Post-Marketing Experience: Cases of sleep disorders and behavior changes have been reported (see PRECAUTIONS, Neuropsychiatric Events). Rash and urticaria have been also reported with ZYFLO.

OVERDOSAGE

Human experience of acute overdose with zileuton is limited. A patient in a clinical trial took between 6.6 and 9.0 grams of zileuton in a single dose. Vomiting was induced and the patient recovered without sequelae. Zileuton is not removed by dialysis. Should an overdose occur, the patient should be treated symptomatically and supportive measures instituted as required. If indicated, elimination of unabsorbed drug should be achieved by emesis or gastric lavage; usual precautions should be observed to maintain the airway. A Certified Poison Control Center should be consulted for up-to-date information on management of overdose with ZYFLO.

The oral minimum lethal doses in mice and rats were 500-4000 and 300-1000 mg/kg in various preparations, respectively (providing greater than 3 and 9 times the systemic exposure [AUC] achieved at the maximum recommended human daily oral dose, respectively). No deaths occurred, but nephritis was reported in dogs at an oral dose of 1000 mg/kg (providing in excess of 12 times the systemic exposure [AUC] achieved at the maximum recommended human daily oral dose).

DOSAGE AND ADMINISTRATION

The recommended dosage of ZYFLO for the symptomatic treatment of patients with asthma is one 600-mg tablet four times a day for a total daily dose of 2400 mg. For ease of administration, ZYFLO may be taken with meals and at bedtime. Hepatic transaminases should be evaluated prior to initiation of ZYFLO and periodically during treatment (see PRECAUTIONS, Hepatic).

HOW SUPPLIED

ZYFLO Tablets are available as 1 dosage strength: 600-mg white to off white, ovaloid, film coated tablets debossed “CT 1” on one side and bisect on the other side.

High-density polyethylene bottles of: 120 Tablets.....................................................................................NDC 10122-901-12

Recommended storage: Store tablets at controlled room temperature between 20˚-25˚C, (68˚-77˚F). See USP. Protect from light.

CTZI-003-0314-01-SPL-3

Manufactured for:

Chiesi USA, Inc.

Cary, NC 27518

Patient Information Leaflet

ZYFLO®

(zileuton tablets)

Patient Information Leaflet

ZYFLO® Tablets

Generic Name: zileuton

Please read this leaflet carefully before you start taking ZYFLO® tablets. Also, read it each time you get your ZYFLO prescription refilled.

This leaflet provides important information about taking ZYFLO. It is not meant to take the place of your doctor’s specific instructions. Talk to your doctor if you have any questions about ZYFLO. Your doctor or pharmacist can also provide you with additional information about ZYFLO.

What is the most important information I should know about ZYFLO?

The most important things to remember are to take all your doses of ZYFLO every day and to make sure that you return to your doctor’s office for scheduled liver enzyme tests.

You should also know that you should seek medical help immediately if you need more “puffs” of your bronchodilator inhaler than normal or if you use the maximum number of “puffs” prescribed for one 24-hour period. These could be a sign of worsening asthma which means that your asthma therapy may need to be changed.

What is ZYFLO?

ZYFLO, which contains the active ingredient zileuton, blocks the formation of certain chemicals (leukotrienes) that may contribute to your asthma symptoms.

Who should not take ZYFLO?

You should not take ZYFLO if you:

- have active liver disease or have liver enzymes that are elevated.
- have ever had an allergic reaction to this medicine.

Your doctor will determine if it is safe for you to take ZYFLO.

What should I tell my doctor before I take the first dose of ZYFLO?

You should tell your doctor if you:

- have ever had liver disease, hepatitis, jaundice (yellow eyes or skin), or dark urine.
- drink alcohol.
- are taking any prescription or nonprescription medicines. Your doctor may adjust the doses of some of your other medicines while you are taking ZYFLO.
- if you are taking theophylline for your asthma, the blood-thinning medication warfarin, or the blood-pressure medication propranolol, your doctor may need to change the doses of these drugs.
- are pregnant, planning to become pregnant, or are breast-feeding.

How should I take ZYFLO?

- ZYFLO is taken four times a day with or without food. It may be easier to remember to take ZYFLO if you make it part of your daily routine such as with meals and at bedtime.
- For ZYFLO to help control your asthma symptoms, it must be taken everyday as prescribed by your doctor. ZYFLO WILL NOT relieve an asthma attack that has already started. While taking ZYFLO, it is important to keep taking your other asthma medicines as directed and to follow all of your doctor’s instructions.
- Even if you have no asthma symptoms, do not decrease the dose of ZYFLO or stop taking the medicine without talking to your doctor first. Feeling good is a sign that the medicine is working.
- When you take your dose of ZYFLO, the tablets may be swallowed whole or split in half to make them easier to swallow.

What should I avoid while taking ZYFLO?

- Because ZYFLO may affect how other medications work, always talk to your doctor before you start or stop taking any medicines while taking ZYFLO. This includes all prescription and nonprescription medicines.
- Never take a larger dose of ZYFLO or take it more often than your doctor has prescribed.
- It is also important for you to know that it may take several days or a few weeks to get the full benefit from ZYFLO and that you should not stop taking it if you do not feel better right away.

What are the possible side effects of ZYFLO?

All medicines, including ZYFLO, cause side effects in some people. Some of the most common side effects are abdominal pain, upset stomach, and nausea. You should tell your doctor if you experience any new or unusual symptoms while taking ZYFLO.

One side effect that occurs in a small number of patients is an increased release of substances from the liver called “enzymes.” Liver enzymes can be measured by a simple blood test. It is important that your doctor makes sure that your liver enzymes do not become too high and that it is safe for you to continue taking ZYFLO. To insure your safety, your doctor will do this blood test before you first start taking ZYFLO and repeat it on a regular basis while you are taking the medicine.

Usually, even if your liver enzymes are increased, you will not notice any symptoms. However, some symptoms of increased liver enzymes are feeling more tired than normal, “flu-like” symptoms, itching, yellow skin, and/or yellow color in the whites of the eyes, or urine that is darker than normal.

Sleep problems and changes in your behavior can happen while you take ZYFLO. Tell your healthcare provider if you have any sleep problems or changes in behavior.

If you notice these or any other symptoms that you think may be caused by ZYFLO, call your doctor immediately. Once the medicine is stopped, these symptoms usually go away.

Even if you do not have any of these symptoms, you should continue to see your doctor for regular check-ups and liver enzyme tests.

Where should I keep my supply of ZYLFO?

Keep ZYFLO and all medicines out of the reach of children. In case of an accidental overdose, call your doctor or a Poison Control Center immediately.

Protect ZYFLO from light and replace the child-resistant cap each time after use. Store ZYFLO between 68◦ - 77◦ F (20◦ - 25◦C).

If you would like more information about ZYFLO, ask your doctor or pharmacist. If you have any questions or concerns about taking ZYFLO, discuss them with your doctor.

Revised: January 2017